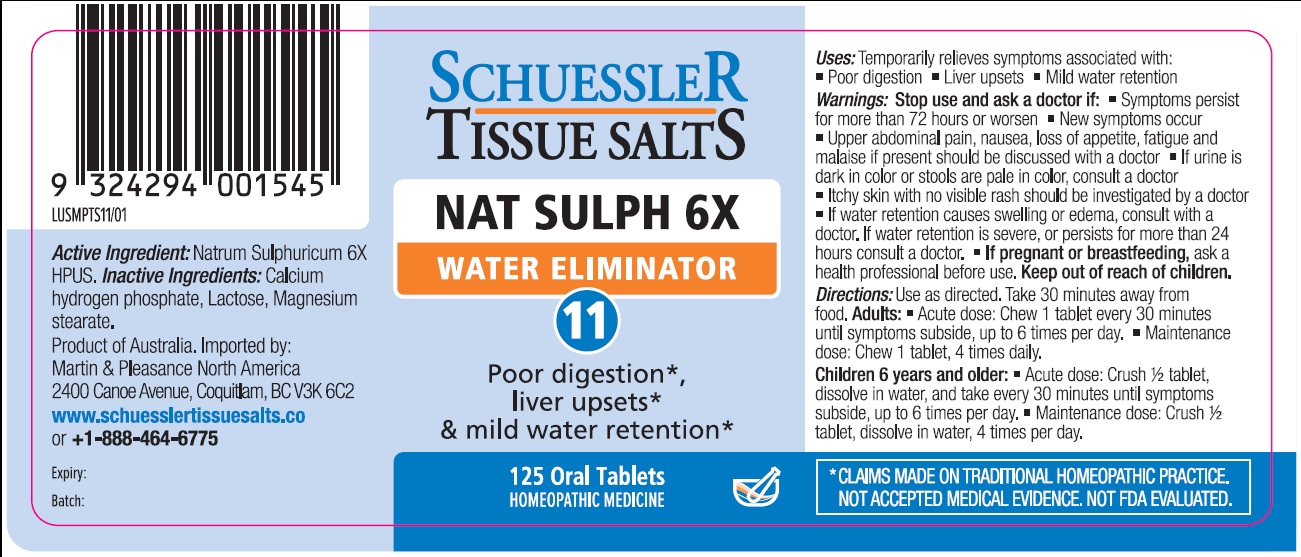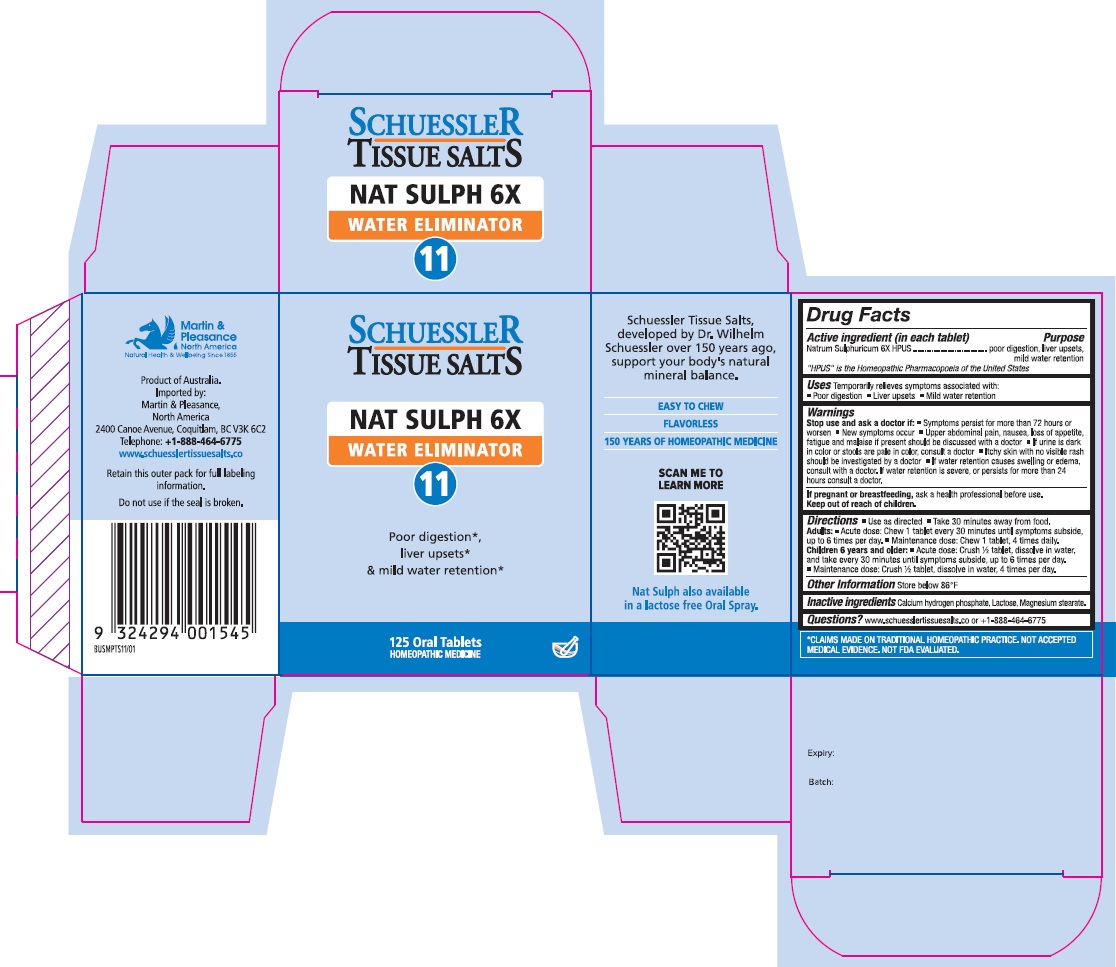 DRUG LABEL: Schuessler Tissue Salts Nat Sulph Water Eliminator 11
NDC: 84999-023 | Form: TABLET, CHEWABLE
Manufacturer: Martin & Pleasance Pty Ltd
Category: homeopathic | Type: HUMAN OTC DRUG LABEL
Date: 20250804

ACTIVE INGREDIENTS: SODIUM SULFATE ANHYDROUS 6 [hp_X]/1 1
INACTIVE INGREDIENTS: LACTOSE MONOHYDRATE; MAGNESIUM STEARATE; ANHYDROUS DIBASIC CALCIUM PHOSPHATE

Active Ingredients Purpose

Natrum Sulphuricum 6X HPUS poor digestion, liver upsets, mild water retention.

" HPUS" is the Homeopathic Pharmacopoeia of the United States

Uses

Temporarily relieves symptoms associated with

- Poor digestion
- Liver upsets,
- Mild water retention

Warnings

Stop use and ask a doctor if:

- Symptoms persist for more than 72 hours or worsen
- New symptoms occur
- Upper abdominal pain, nausea, loss of appetite, fatigue, or malaise if present should be discussed with a doctor
- If urine is dark in color or stools are pale in color, consult a doctor
- Itchy skin with no visible rash should be investigated by a doctor
- If water retention causes swelling or edema, consult with a doctor
- If water retention is severe, or persists for more than 24 hours consult a doctor

If pregnant or breastfeeding, ask a health professional before use.

Keep out of reach of children.

Directions

- Use as directed
- Take 30 minutes away from food

Adults: Acute dose: Chew 1 tablet every 30 minutes until symptoms subside up to 6 times per day.

Maintenance dose: Chew 1 tablet, 4 times daily.

Children 6 years and older: Acute dose: Crush 1/2 tablet, dissolve in water, and take every 30 minutes until symptoms subside, up to six times per day.

Maintenance dose :Crush 1/2 tablet, dissolve in water, 4 times per day.

Other Information

Store below 86°F

Inactive Ingredients

Calcium hydrogen phosphate, Lactose, Magnesium stearate

Questions?www.schuesslertissuesalts.co or + 1-888-464-6775